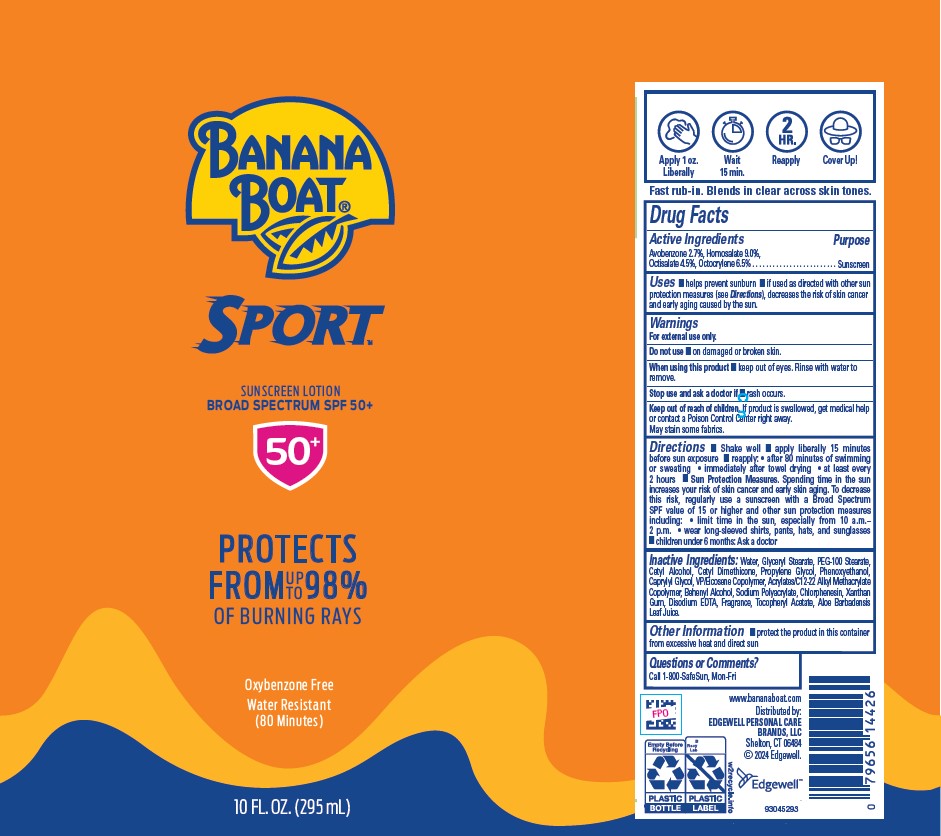 DRUG LABEL: BANANA BOAT
NDC: 63354-896 | Form: LOTION
Manufacturer: Edgewell Personal Care Brands LLC
Category: otc | Type: HUMAN OTC DRUG LABEL
Date: 20241027

ACTIVE INGREDIENTS: OCTISALATE 4.5 g/100 g; AVOBENZONE 2.7 g/100 g; OCTOCRYLENE 6.5 g/100 g; HOMOSALATE 9 g/100 g
INACTIVE INGREDIENTS: WATER; EDETATE DISODIUM; SODIUM POLYACRYLATE (2500000 MW); PHENOXYETHANOL; .ALPHA.-TOCOPHEROL ACETATE; CHLORPHENESIN; XANTHAN GUM; GLYCERYL MONOSTEARATE; ALOE VERA LEAF; CETYL ALCOHOL; PROPYLENE GLYCOL; CAPRYLYL GLYCOL; VINYLPYRROLIDONE/EICOSENE COPOLYMER; PEG-100 STEARATE; DOCOSANOL

Active Ingredients

Avobenzone 2.7%, Homosalate 9.0%,Octisalate 4.5%, Octocrylene 6.5%

Purpose

Sunscreen

Uses

•helps prevent sunburn • if used as directed with other sun protection measures (see Directions), decreases the risk of skin cancer and early aging caused by the sun.

Warnings

For external use only.

May stain some fabrics.

Do not use

•on damaged or broken skin.

When using this product

•keep out of eyes. Rinse with water to remove.

Stop use and ask a doctor if

• rash occurs.

Keep out of reach of children.

If product is swallowed, get medical help or contact a Poison Control Center right away.

Directions

• Shake well • apply liberally 15 minutes before sun exposure • reapply: • after 80 minutes of swimming or sweating • immediately after towel drying • at least every 2 hours • Sun Protection Measures. Spending time in the sun increases your risk of skin cancer and early skin aging. To decrease this risk, regularly use a sunscreen with a Broad Spectrum SPF value of 15 or higher and other sun protection measures including: • limit time in the sun, especially from 10 a.m.– 2 p.m. • wear long-sleeved shirts, pants, hats, and sunglasses • children under 6 months: Ask a doctor

Inactive Ingredients:

Water, Glyceryl Stearate, PEG-100 Stearate, Cetyl Alcohol, Cetyl Dimethicone, Propylene Glycol, Phenoxyethanol, Caprylyl Glycol, VP/Eicosene Copolymer, Acrylates/C12-22 Alkyl Methacrylate Copolymer, Behenyl Alcohol, Sodium Polyacrylate, Chlorphenesin, Xanthan Gum, Disodium EDTA, Fragrance, Tocopheryl Acetate, Aloe Barbadensis Leaf Juice.

Other Information

• protect the product in this container from excessive heat and direct sun

Questions or Comments?

Call 1-800-SafeSun, Mon-Fri

PRINCIPAL DISPLAY PANEL

BANANA

BOAT

SPORT

SUNSCREEN LOTION

BROAD SPECTRUM SPF 50+

50+

PROTECTS

FROM UP TO 98%

OF BURNING RAYS

OXYBENZONE FREE

WATER RESISTANT

(80 MINUTES)

10 FL OZ (295 mL)